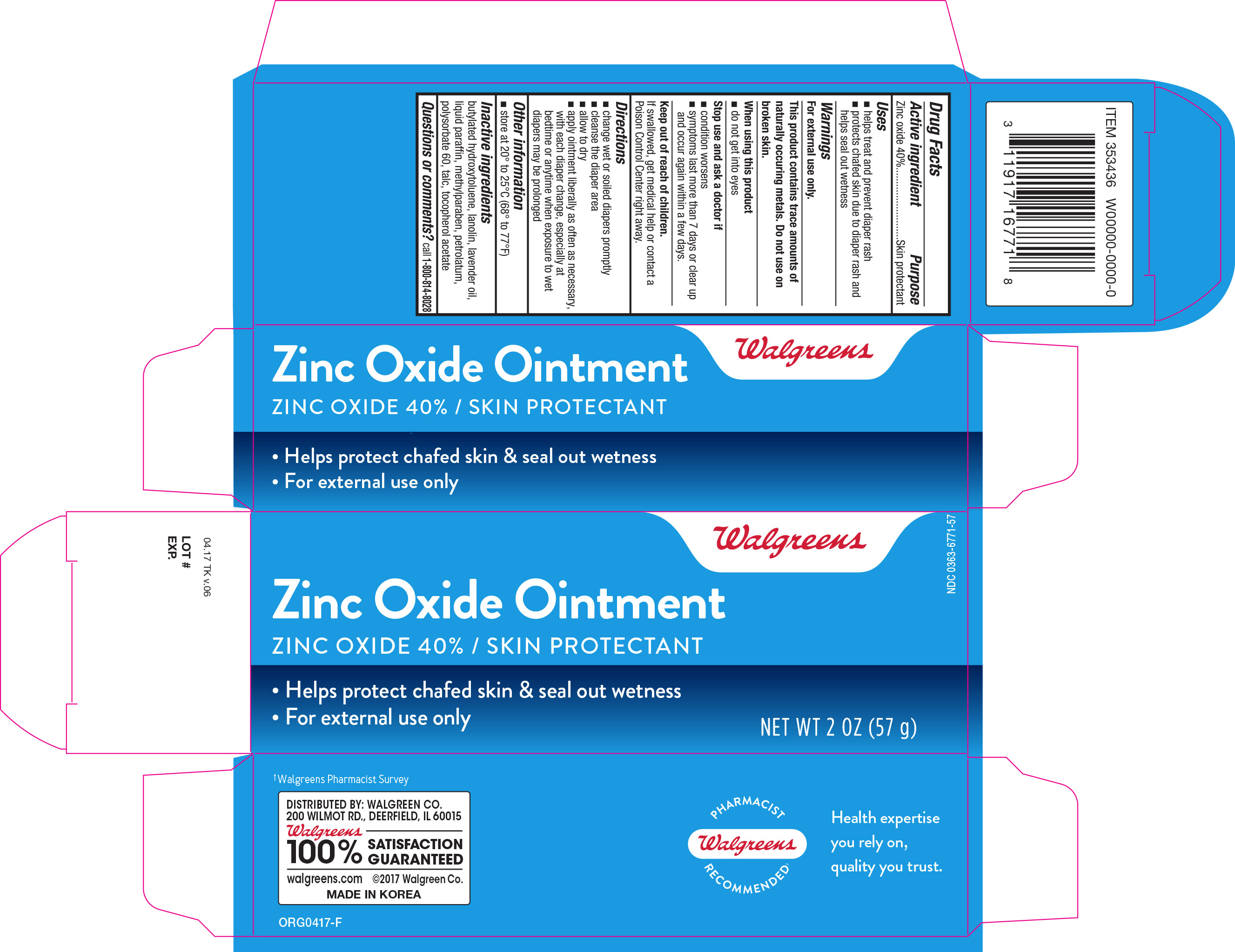 DRUG LABEL: Walgreens Zinc Oxide
NDC: 0363-6771 | Form: OINTMENT
Manufacturer: Walgreen Company
Category: otc | Type: HUMAN OTC DRUG LABEL
Date: 20180301

ACTIVE INGREDIENTS: ZINC OXIDE 40 g/100 g
INACTIVE INGREDIENTS: BUTYLATED HYDROXYTOLUENE; LAVENDER OIL; PARAFFIN; METHYLPARABEN; PETROLATUM; POLYSORBATE 60; LANOLIN; TALC; .ALPHA.-TOCOPHEROL ACETATE; WATER

Walgreens Zinc Oxide Ointment 2oz (353436) 2018

Active Ingredient Purpose

Zinc oxide 40%.............................................Skin protectant

Uses

- helps treat and prevent diaper rash
- protects chafed skin due to diaper rash and helps seal out wetness

Warnings

For external use only.

This product contains trace amounts of naturally occurring metals. Do not use on broken skin

When using this product

- do not get into eyes

Stop use and ask a doctor if

- condition worsens
- symtoms last more than 7 days or clear up and occur again within a few days.

Keep out of the reach of children.

If swallowed, get medical help or contact a Poison Control Center right away.

Directions

- change wet or soiled diapers promptly
- clean the diaper area
- allow to dry
- apply ointment liberally as often as necessary, with each diaper change, especially at bedtime or anytime when exposure to wet diapers may be prolonged.

Other Information

store at 20°C to 25°C (68° to 77°F)

Inactive ingredients

butylated hydroxytoluene, lanolin, lavender oil, liquid paraffin, methylparaben, petrolatum, polysorbate 60, talc, tocopherol acetate

DOSAGE AND ADMINISTRATION

Distributed by:

Walgreen Co.

299 Wilmot Rd.,

Deerfield, IL 60015 USA

Made in Korea